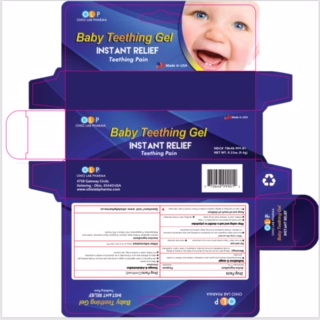 DRUG LABEL: OLP Baby Teething
NDC: 70648-999 | Form: GEL
Manufacturer: Ohio Lab Pharma
Category: otc | Type: HUMAN OTC DRUG LABEL
Date: 20200401

ACTIVE INGREDIENTS: BENZOCAINE 7.5 g/100 g
INACTIVE INGREDIENTS: WATER; SORBIC ACID; FD&C RED NO. 40; PROPYLPARABEN; METHYLPARABEN; CARBOMER 940; PROPYLENE GLYCOL; FD&C YELLOW NO. 5; SORBITOL; GLYCERIN

Uses

- temporarily relieves sore gums due to teething in infants and children 4 months of age and older

Warnings

- Allergy alert: do not use this product if you have a history of allergy to local anesthetics such as

procaine, butacaine, benzocaine or other “caine” anesthetics

- Do not use more than directed for more than 7 days unless told to do so by a dentist or doctor.
- When using this product fever and nasal congestion are not symptoms of teething and may indicate the presence of infection. If these symptoms do not go away, advise your dentist or doctor.
- Stop use and ask a doctor if sore mouth symptoms do not get better in 7 days. swelling, rash or fever develops, irritation, pain or redness persists or worsens
- Keep out of reach of children. In case of overdose, get medical help or contact a Poison Control Center right away.

Purpose

anaesthetic

Active Ingredient

Benzocaine 7.5%

Other information

store at 15 to 25 C(59-77F)

Directions

- wash hands
- cut open tip of tube on score mark
- use your fingertip or cotton applicator to apply a small pea-size amount of baby teething gel
- apply to affected area up to four times daily or as directed by a dentist or doctor

for infants under 4 months of age, ask a dentist or doctor

Inactive ingredients

FD&C yellow 5, FD&C Red 40, Flavor, Glycerin, Poropylene Glycols, Purified Water, Sorbic Acid, , carbomer, methyl paraben, propyl paraben

when using this product

Fever and nasal congestion are not symptoms of teething and may indicate the presence of infection. If these symptoms do not go away. advise your physician

stop using and ask a dentist or physician

- sore mouth symptoms do not get better in 7 days
- irritation, pain or redness does not go away
- swelling, rash or fever develops

keep out of reach of children

in case of overdose or allergic reaction contact a poison control center right away

questions

www.ohiolabpharma.us

PACKAGE LABEL

NET WEIGHT 0.33 oz (9.4g)

NDC#70648-999-01